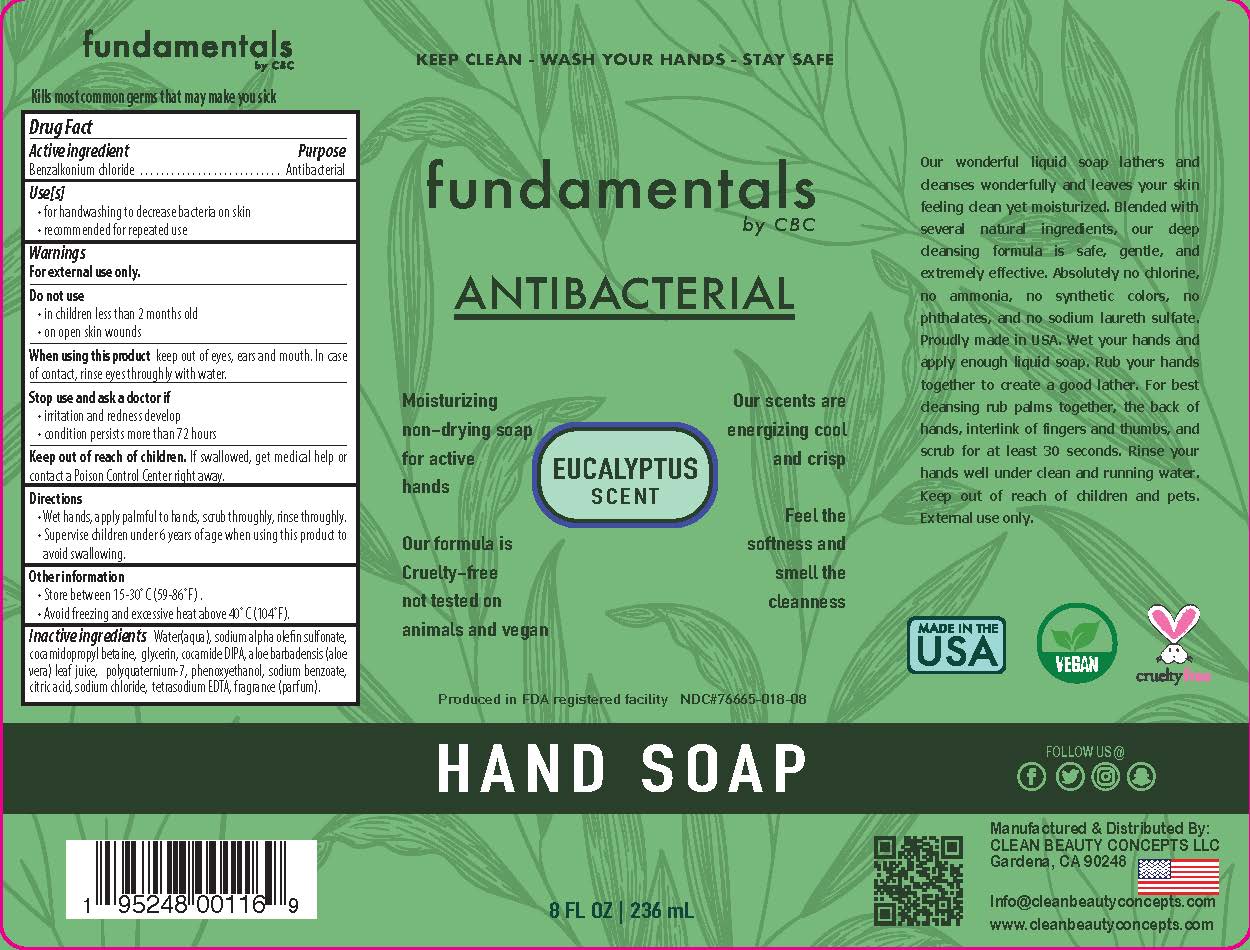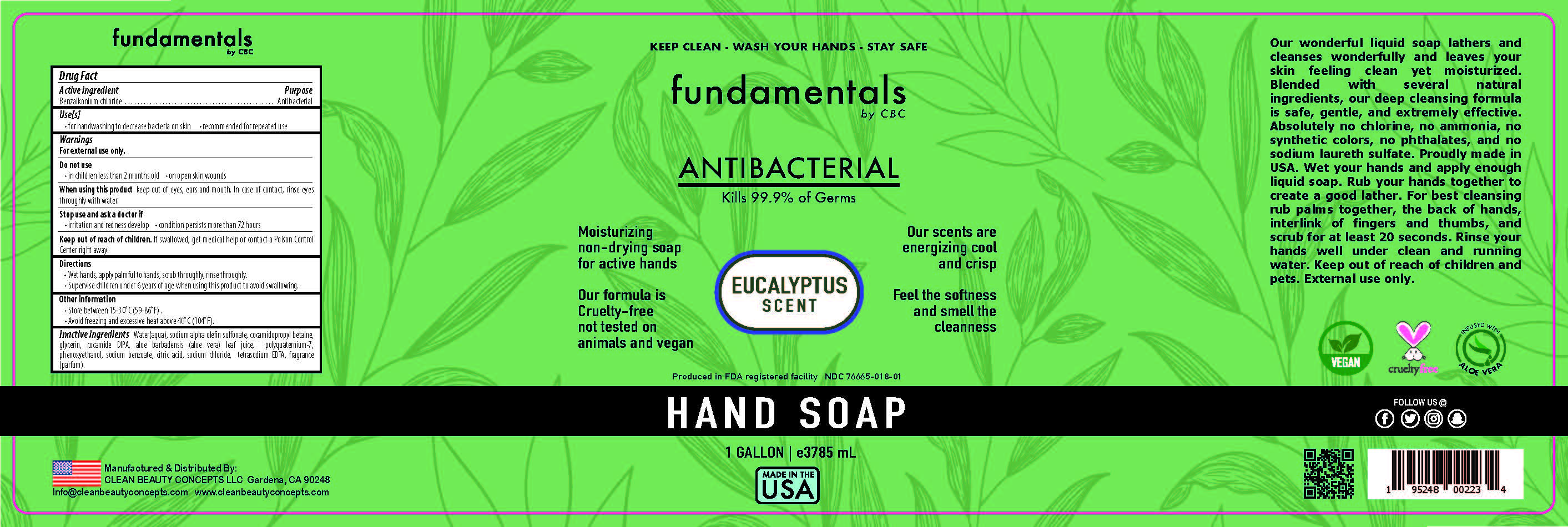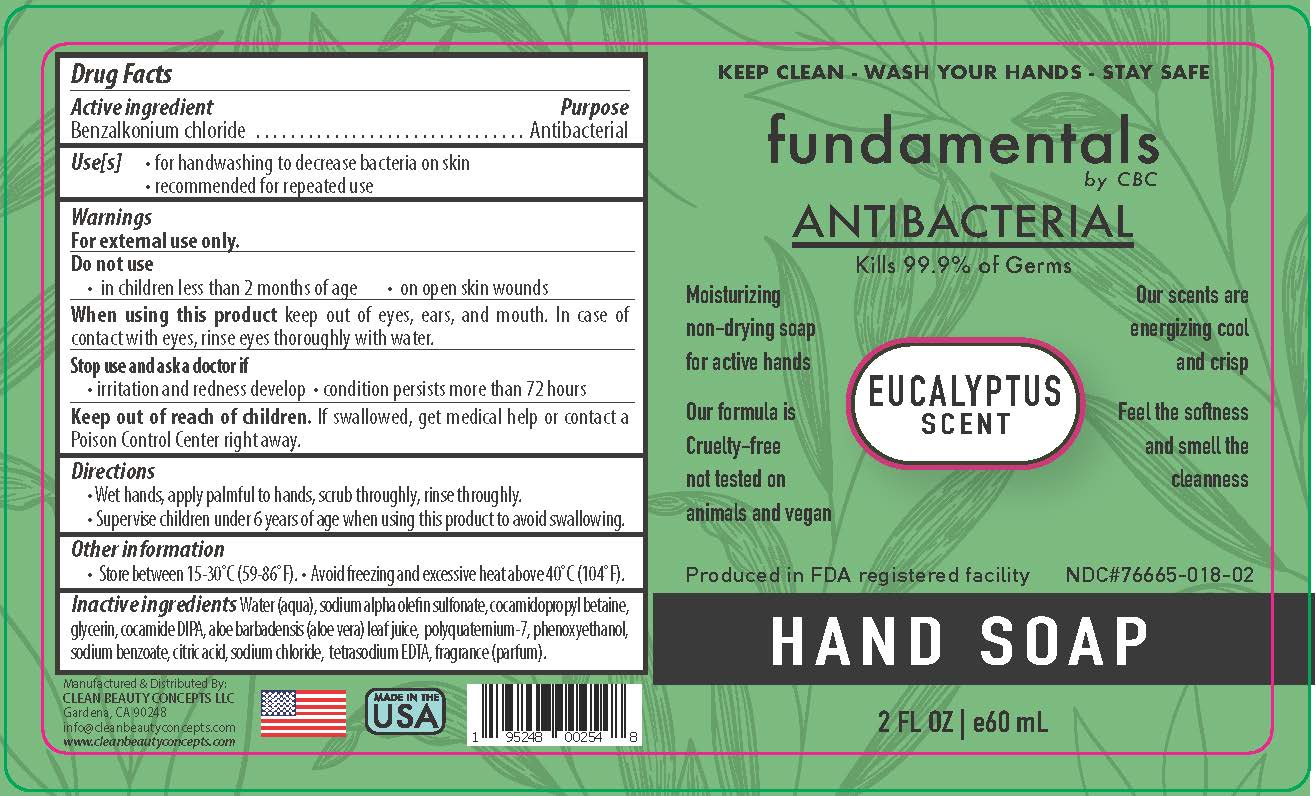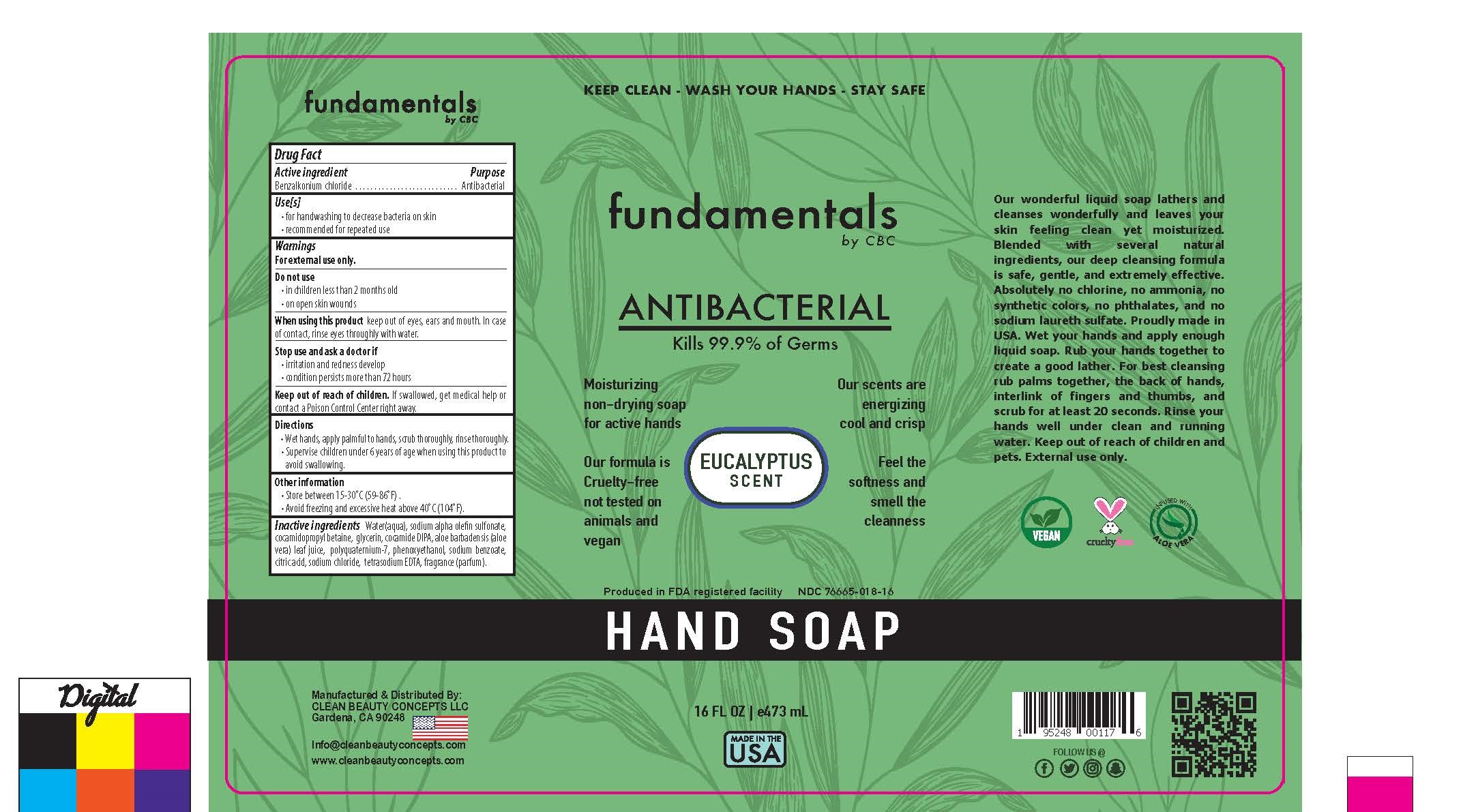 DRUG LABEL: Fundamentals
NDC: 76665-018 | Form: SOAP
Manufacturer: Clean Beauty Concepts
Category: otc | Type: HUMAN OTC DRUG LABEL
Date: 20201016

ACTIVE INGREDIENTS: BENZALKONIUM CHLORIDE 0.13 mg/100 mL
INACTIVE INGREDIENTS: POLYQUATERNIUM-7 (70/30 ACRYLAMIDE/DADMAC; 1600000 MW) 0.35 mL/100 mL; PHENOXYETHANOL 0.3 mL/100 mL; SODIUM CHLORIDE 0.15 mL/100 mL; EUCALYPTUS OIL 0.1 mL/100 mL; WATER 75.71 mL/100 mL; COCAMIDOPROPYL BETAINE 3.42 mL/100 mL; EDETATE SODIUM 0.01 mL/100 mL; GLYCERIN 0.35 mL/100 mL; SODIUM BENZOATE 0.1 mL/100 mL; DISODIUM ETHYLENE DICOCAMIDE PEG-15 DISULFATE 8.47 mL/100 mL; ALOE VERA LEAF POLYSACCHARIDES 0.1 mL/100 mL; ANHYDROUS CITRIC ACID 0.02 mL/100 mL; SODIUM C12 OLEFIN SULFONATE 10.79 mL/100 mL

The hand soap is manufactured using only the following United States Pharmacopoeia (USP) grade ingredients:

Benzalkonium chloride

Water(aqua)

Sodium alpha olefin sulfonate

Cocamide DIPA

Cocamidopropyl betaine

Glycerin

Polyquaternium-7

Phenoxyethanol

Aloe barbadensis (aloe vera) leaf juice

Sodium benzoate

Citric acid

Sodium chloride

Tetrasodium EDTA

Fragrance (parfum)

Active Ingredient(s)

Benzalkonium chloride 0.13% v/v. Purpose: Antibacterial

Purpose

Antibacterial

Use

For handwashing to decrease bacteria on skin

Recommended for repeat use

Warnings

For external use only.

When using this product keep out of eyes, ears, and mouth. In case of contact with eyes, rinse eyes thoroughly with water.

Stop use and ask a doctor if

irritation or redness develop

Condition persists more than 72 hours

Keep out of reach of children. If swallowed, get medical help or contact a Poison Control Center right away.

Directions

• Wet hands, apply palmful to hands, scrub thoroughly, rinse thoroughly

- Supervise children under 6 years of age when using this product to avoid swallowing

Other information

- Store between 15-30°C (59-86°F) .
  • Avoid freezing and excessive heat above 40°C (104°F).

Inactive ingredients

Water(aqua)

Sodium alpha olefin sulfonate

Cocamide DIPA

Cocamidopropyl betaine

Glycerin

Polyquaternium-7

Phenoxyethanol

Aloe barbadensis (aloe vera) leaf juice

Sodium benzoate

Citric acid

Sodium chloride

Tetrasodium EDTA

Fragrance (parfum)

Package Label - Principal Display Panel

236 mL NDC: 76665-018-08

473mL NDC: 76665-018-16

60mL NDC: 76665-018-02

3785mL NDC: 76665-018-01